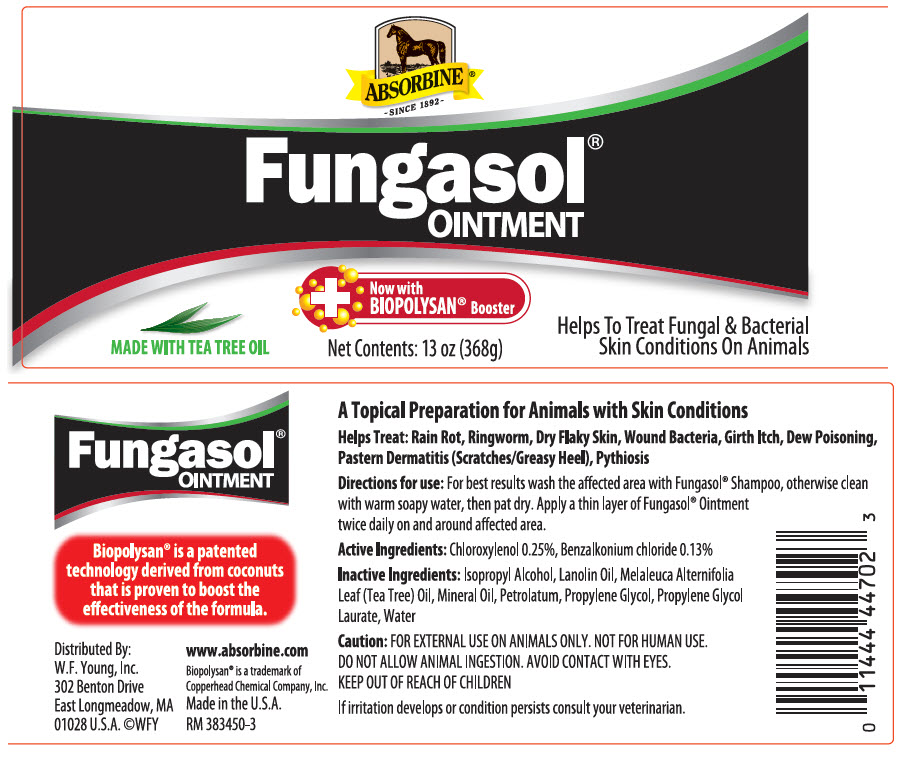 DRUG LABEL: Absorbine Fungasol
NDC: 11444-447 | Form: OINTMENT
Manufacturer: W. F. Young, Inc.
Category: animal | Type: OTC ANIMAL DRUG LABEL
Date: 20210614

ACTIVE INGREDIENTS: CHLOROXYLENOL 0.25 g/100 g; BENZALKONIUM CHLORIDE 0.13 g/100 g

Fungasol®
OINTMENT

Biopolysan® is a patented technology derived from coconuts that is proven to boost the effectiveness of the formula.

DESCRIPTION

A Topical Preparation for Animals with Skin Conditions

Helps Treat: Rain Rot, Ringworm, Dry Flaky Skin, Wound Bacteria, Girth Itch, Dew Poisoning, Pastern Dermatitis (Scratches/Greasy Heel), Pythiosis

DOSAGE AND ADMINISTRATION

Directions for use: For best results wash the affected area with Fungasol® Shampoo, otherwise clean with warm soapy water, then pat dry. Apply a thin layer of Fungasol® Ointment twice daily on and around affected area.

Active Ingredients: Chloroxylenol 0.25%, Benzalkonium chloride 0.13%

Inactive Ingredients: Isopropyl Alcohol, Lanolin Oil, Melaleuca Alternifolia Leaf (Tea Tree) Oil, Mineral Oil, Petrolatum, Propylene Glycol, Propylene Glycol Laurate, Water

PRECAUTIONS

Caution: FOR EXTERNAL USE ON ANIMALS ONLY.

NOT FOR HUMAN USE. DO NOT ALLOW ANIMAL INGESTION.

AVOID CONTACT WITH EYES. KEEP OUT OF REACH OF CHILDREN

If irritation develops or condition persists consult your veterinarian.

Distributed By:
W.F. Young, Inc.
302 Benton Drive
East Longmeadow, MA
01028 U.S.A. ©WFY
www.absorbine.com

Biopolysan® is a trademark of
Copperhead Chemical Company, Inc.

Made in the U.S.A.

RM 383450

PRINCIPAL DISPLAY PANEL - 368 g Jar Label

ABSORBINE®
~SINCE 1892~

Fungasol®
OINTMENT

+
Now with
BIOPOLYSAN® Booster

MADE WITH TEA TREE OIL

Net Contents: 13 oz (368g)

Helps To Treat Fungal & Bacterial
Skin Conditions On Animals